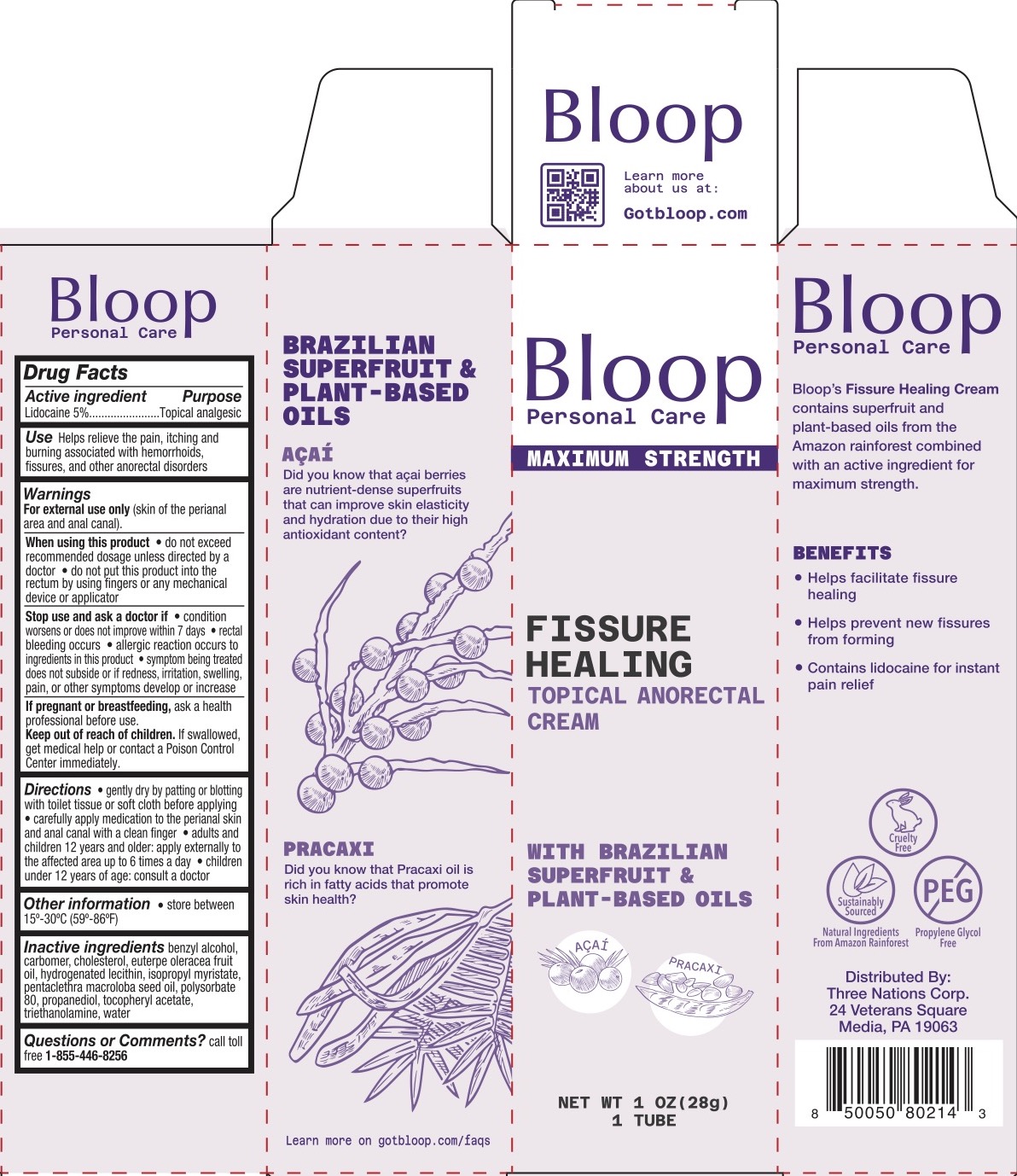 DRUG LABEL: Bloop Fissure Healing Anorectal Topical
NDC: 83838-153 | Form: CREAM
Manufacturer: Three Nations Corp
Category: otc | Type: HUMAN OTC DRUG LABEL
Date: 20231130

ACTIVE INGREDIENTS: LIDOCAINE 5 g/100 g
INACTIVE INGREDIENTS: CARBOMER 940; BENZYL ALCOHOL; CHOLESTEROL; ACAI OIL; EDETATE DISODIUM; HYDROGENATED SOYBEAN LECITHIN; PROPANEDIOL; ISOPROPYL MYRISTATE; PENTACLETHRA MACROLOBA SEED OIL; POLYSORBATE 80; .ALPHA.-TOCOPHEROL ACETATE; WATER; TROLAMINE

Bloop Fissure Healing Topical Anorectal Cream

ACTIVE INGREDIENT

Lidocaine 5%

PURPOSE

Anorectal (hemorrhoidal)

INDICATIONS AND USAGE

- Helps relieve the pain, itching, and burning associated with hemorrhoids, fissures, and other anorectal disorders

WARNINGS

For external use only (skin of the perianal area and anal canal).

When using this product

- do not exceed recommended dosage unless directed by a doctor
- do not put this product into the rectum by using fingers or any mechanical device or applicator

Stop use and ask a doctor if

- condition worsens or does not improve within 7 days
- rectal bleeding occurs
- allergic reaction occurs to ingredients in this product
- symptom being treated does not subside or if redness, irritation, swelling, pain, or other symptoms develop or increase

PREGNANCY OR BREAST FEEDING

Ask a health professional before use.

KEEP OUT OF REACH OF CHILDREN

If swallowed, get medical help or contact a Poison Control Center immediately.

DOSAGE AND ADMINISTRATION

- Gently dry by patting or blotting with toilet tissue or soft cloth before applying
- Carefully apply medication to the perianal skin and anal canal with a clean finger
- Adults and children 12 years and older: apply externally to the affected area up to 6 times a day
- Children under 12 years of age consult a doctor

INACTIVE INGREDIENT

Benzyl alcohol, carbomer, cholesterol, euterpe oleracea fruit oil, hydrogenated lecithin, isopropyl myristate, pentaclethra macroloba seed oil, polysorbate 80, propanediol, tocopheryl acetate, triethanolamine, water.